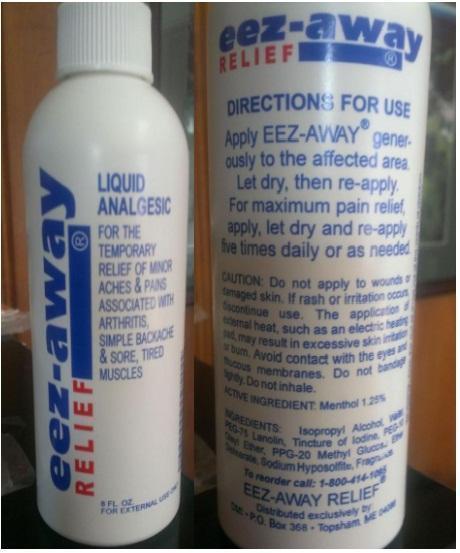 DRUG LABEL: eez-away RELIEF
NDC: 69678-101 | Form: SPRAY
Manufacturer: EEZAWAY RELIEF INC
Category: otc | Type: HUMAN OTC DRUG LABEL
Date: 20170606

ACTIVE INGREDIENTS: MENTHOL 1.25 g/100 mL
INACTIVE INGREDIENTS: WATER; ALCOHOL; IODINE; ISOPROPYL ALCOHOL; POLYOXYL-10 OLEYL ETHER; PEG-75 LANOLIN; PPG-20 METHYL GLUCOSE ETHER DISTEARATE; SODIUM IODIDE; SODIUM THIOSULFATE

eez-away RELIEF

ACTIVE INGREDIENT:

Menthol 1.25%

PURPOSE

Liquid Analgesic

Keep out of reach of children.

INDICATIONS AND USAGE

FOR THE TEMPORARY RELIEF OF MINOR ACHES & PAINS ASSOCIATED WITH ARTHRITIS, SIMPLE BACKACHE & SORE, TIRED MUSCLES.

PRECAUTIONS

CAUTION: Do not apply to wounds or damaged skin. If rash or irritation occurs, discontinue use.

WARNINGS

The application of external heat, such as an electric heating pad, may result in excessive skin irritation or burn. Avoid contact with the eyes and mucous membranes. Do not bandage tightly. Do not inhale.

DIRECTIONS FOR USE

Apply EEZ-AWAY® generously to the affected area. Let dry, then re-apply. For maximum pain relief, apply, let dry and re-apply five times daily or as needed.

INACTIVE INGREDIENT

INGREDIENTS: Isopropyl Alcohol, Deionized Water (Aqua), PEG-75 Lanolin, Iodine, Oleth-10, PPG-20 Methyl Glucose Ether Distearate, Sodium Iodide, Sodium Thiosulfate, Ethyl Alcohol, Fragrance.

QUESTIONS

To reorder call: 302-339-3030